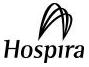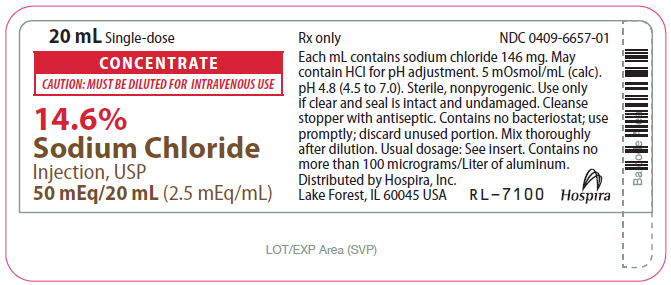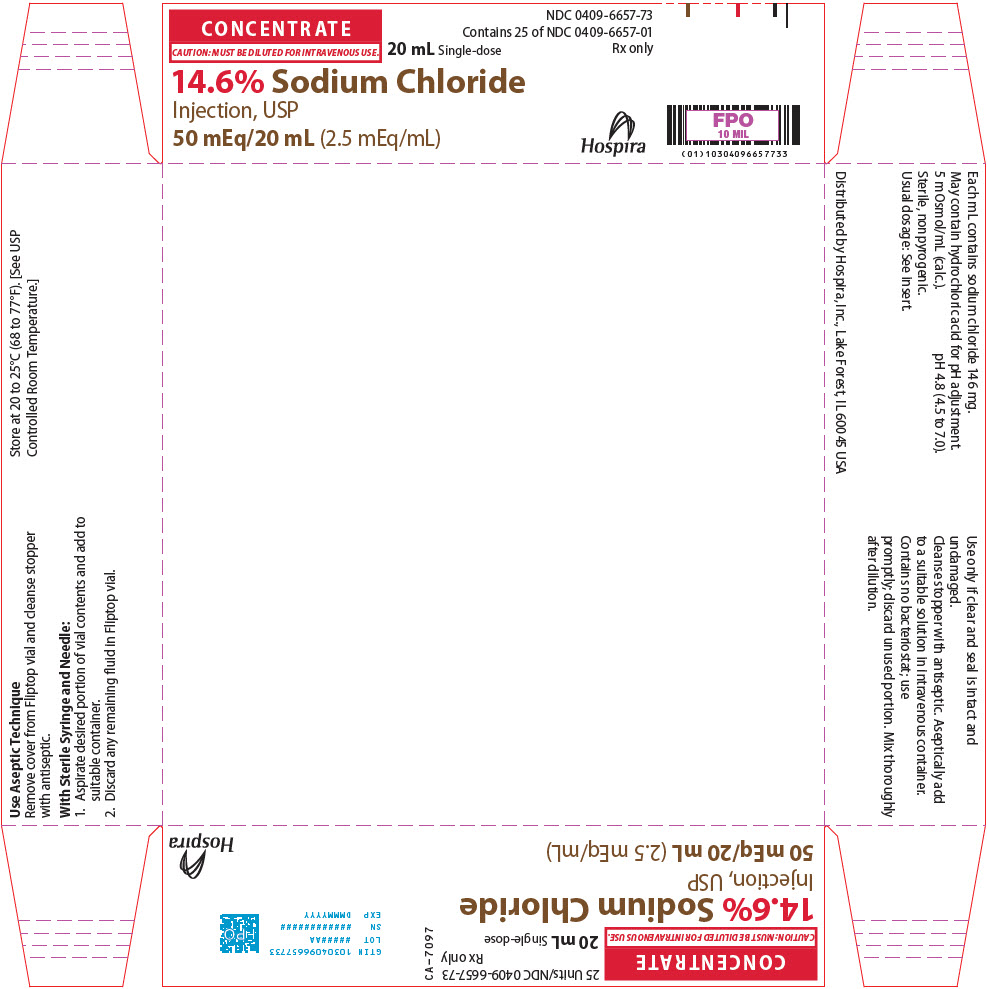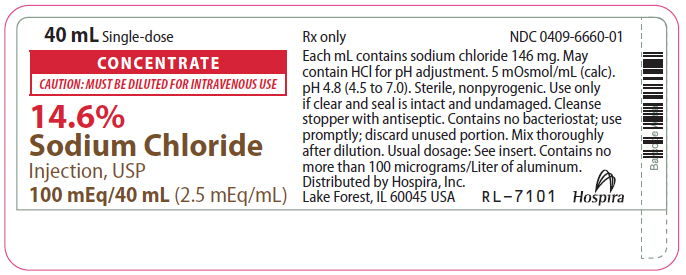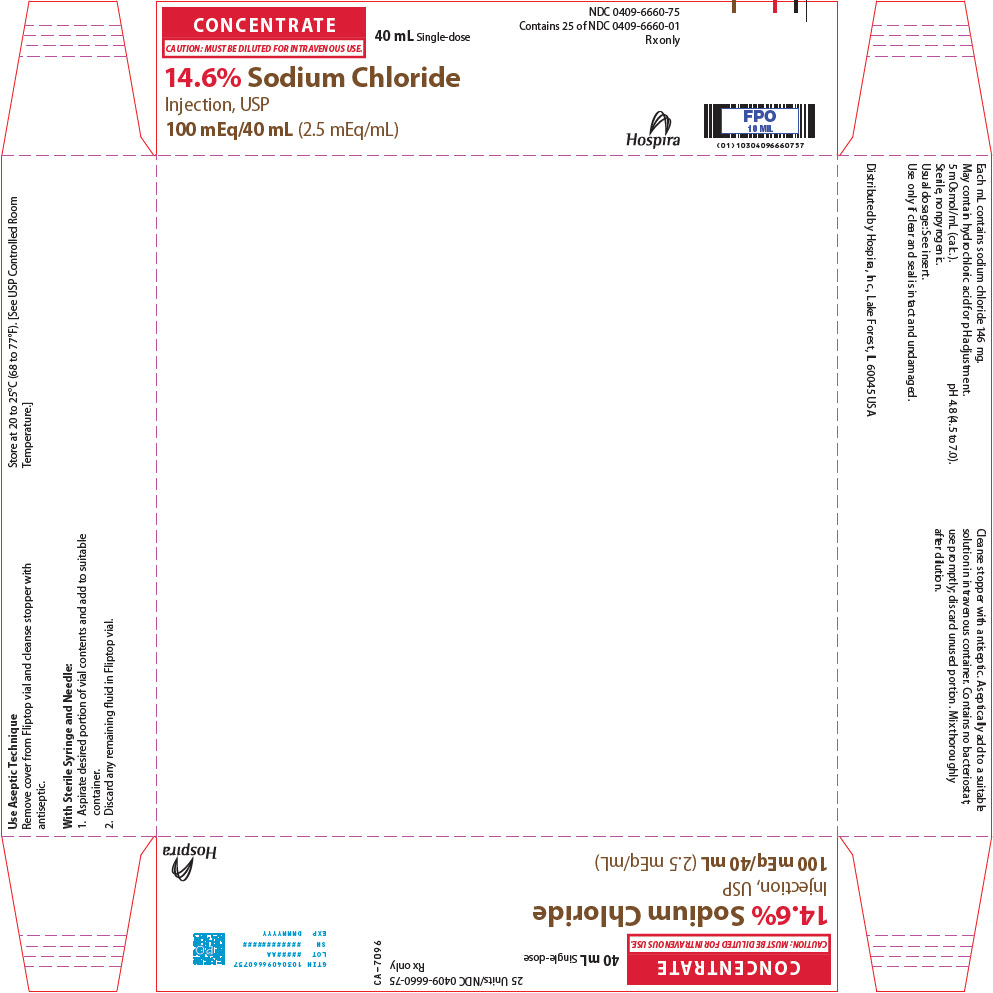 DRUG LABEL: Sodium Chloride
NDC: 0409-6657 | Form: INJECTION, SOLUTION, CONCENTRATE
Manufacturer: Hospira, Inc.
Category: prescription | Type: HUMAN PRESCRIPTION DRUG LABEL
Date: 20241015

ACTIVE INGREDIENTS: SODIUM CHLORIDE 2.92 g/20 mL
INACTIVE INGREDIENTS: WATER; HYDROCHLORIC ACID

CONCENTRATE

CAUTION: MUST BE DILUTED FOR I.V. USE

14.6%
Sodium Chloride Injection, USP Rx only
50 mEq/20 mL or 100 mEq/40 mL
(2.5 mEq/mL)
Additive Solution
Concentrated Solution —

For use only after dilution with compatible I.V. fluids to correct sodium deficiency when oral replacement is not feasible.

Plastic Vial

DESCRIPTION

14.6% Sodium Chloride Injection, USP Additive Solution is a sterile, nonpyrogenic, concentrated solution for intravenous administration ONLY AFTER DILUTION to replenish electrolytes. The preparations contain either 2.92 or 5.84 g of sodium chloride (50 or 100 mEq each of Na^+ and Cl¯) in Water for Injection, USP. The solution contains no bacteriostat, antimicrobial agent or added buffer; pH 4.8 (4.5 to 7.0). May contain hydrochloric acid for pH adjustment. The osmolar concentration is 5 mOsmol/mL (calc.); specific gravity is 1.10.

Sodium Chloride, USP is chemically designated NaCl, a white crystalline compound freely soluble in water.

The semi-rigid material used for the plastic vials is fabricated from a specially formulated polyolefin. It is a copolymer of ethylene and propylene. The safety of the plastic has been confirmed by tests in animals according to USP biological standards for plastic containers. The container requires no vapor barrier to maintain the proper drug concentration.

CLINICAL PHARMACOLOGY

Sodium chloride in water dissociates to provide sodium (Na^+) and chloride (Cl¯) ions. These ions are normal constituents of the body fluids (principally extracellular) and are essential for maintaining electrolyte balance.

Sodium is the principal cation of extracellular fluid. It comprises more than 90% of the total cations at its normal plasma concentration of approximately 142 mEq/liter. While the sodium ion can diffuse across cell membranes, intracellular sodium is maintained at a much lower concentration than extracellular sodium through the expenditure of energy by the cell (so called "sodium cation pump"). Loss of intracellular potassium ion is usually accompanied by an increase in intracellular sodium ion.

When serum sodium concentration is low, the secretion of antidiuretic hormone (ADH) by the pituitary is inhibited, thereby preventing water reabsorption by the distal renal tubules. On the other hand, adrenal secretion of aldosterone increases renal tubular reabsorption of sodium in an effort to re-establish normal serum sodium concentration.

Chloride (Cl¯) has an integral role in buffering action when oxygen and carbon dioxide exchange occurs in the red blood cells.

The distribution and excretion of sodium (Na^+) and chloride (Cl¯) are largely under the control of the kidney which maintains a balance between intake and output.

INDICATIONS AND USAGE

14.6% Sodium Chloride Injection, USP Additive Solution is indicated for parenteral restoration of sodium ion in patients with restricted oral intake. Sodium replacement is specifically indicated in patients with hyponatremia or low salt syndrome. 14.6% Sodium Chloride Additive Solution may also be added to compatible carbohydrate solutions such as dextrose in water to provide electrolytes.

CONTRAINDICATIONS

14.6% Sodium Chloride Injection, USP Additive Solution is contraindicated in patients with hypernatremia or fluid retention.

WARNINGS

14.6% Sodium Chloride Injection, USP is hypertonic and must be diluted prior to administration. Inadvertent direct injection or absorption of concentrated sodium chloride solution may give rise to sudden hypernatremia and such complications as cardiovascular shock, central nervous system disorders, extensive hemolysis, cortical necrosis of the kidneys and severe local tissue necrosis (if administered extravascularly).

Solutions containing sodium ions should be used with great care, if at all, in patients with congestive heart failure, severe renal insufficiency and in clinical states in which there exists edema with sodium retention.

In patients with diminished renal function, administration of solutions containing sodium may result in sodium retention.

The intravenous administration of this solution (after appropriate dilution) can cause fluid and/or solute overload resulting in dilution of other serum electrolyte concentrations, overhydration, congested states or pulmonary edema.

Excessive administration of potassium free solutions may result in significant hypokalemia.

WARNING: This product contains aluminum that may be toxic. Aluminum may reach toxic levels with prolonged parenteral administration if kidney function is impaired. Premature neonates are particularly at risk because their kidneys are immature, and they require large amounts of calcium and phosphate solutions, which contain aluminum.

Research indicates that patients with impaired kidney function, including premature neonates, who receive parenteral levels of aluminum at greater than 4 to 5 mcg/kg/day accumulate aluminum at levels associated with central nervous system and bone toxicity. Tissue loading may occur at even lower rates of administration.

PRECAUTIONS

14.6% Sodium Chloride Injection, USP Additive Solution must be diluted before infusion to avoid a sudden increase in the level of plasma sodium. Too rapid administration should be avoided.

Special caution should be used in administering sodium containing solutions to patients with severe renal impairment, cirrhosis of the liver, cardiac failure, or other edematous or sodium-retaining states.

Clinical evaluation and periodic laboratory determinations are necessary to monitor changes in fluid balance, electrolyte concentrations, and acid-base balance during prolonged parenteral therapy or whenever the condition of the patient warrants such evaluation.

Caution must be exercised in the administration of parenteral fluids, especially those containing sodium ions, to patients receiving corticosteroids or corticotropin.

Do not use unless the solution is clear and seal is intact. Discard unused portion.

Pregnancy

Animal reproduction studies have not been conducted with sodium chloride. It is also not known whether sodium chloride can cause fetal harm when administered to a pregnant woman or can affect reproduction capacity. Sodium chloride should be given to a pregnant woman only if clearly needed.

Geriatric Use

An evaluation of current literature revealed no clinical experience identifying differences in response between elderly and younger patients. In general, dose selection for an elderly patient should be cautious, usually starting at the low end of the dosing range, reflecting the greater frequency of decreased hepatic, renal, or cardiac function, and of concomitant disease or other drug therapy.

This drug is known to be substantially excreted by the kidney, and the risk of toxic reactions to this drug may be greater in patients with impaired renal function. Because elderly patients are more likely to have decreased renal function, care should be taken in dose selection, and it may be useful to monitor renal function.

Pediatric Use

The safety and effectiveness of 14.6% Sodium Chloride Injection, USP Additive Solution have not been established. Its limited use in pediatric patients has been inadequate to fully define proper dosage and limitations for use.

ADVERSE REACTIONS

Sodium overload can occur with intravenous infusion of excessive amounts of sodium-containing solutions. (See WARNINGS and PRECAUTIONS.)

OVERDOSAGE

In the event of overhydration or solute overload, re-evaluate the patient and institute appropriate corrective measures. (See WARNINGS and PRECAUTIONS.)

DOSAGE AND ADMINISTRATION

14.6% Sodium Chloride Injection, USP Additive Solution is administered intravenously only after addition to a larger volume of fluid.

The dose, dilution and rate of injection are dependent upon the individual needs of each patient.

All or part of the contents of one or more additive containers may be added to an intravenous solution container. Concentrations of up to 5% sodium chloride have been administered.

Parenteral drug products should be inspected visually for particulate matter and discoloration prior to administration, whenever solution and container permit. (See PRECAUTIONS.)

HOW SUPPLIED

14.6% Sodium Chloride Injection, USP Additive Solution is supplied as the following:

Unit of Sale | Concentration | Each
NDC 0409-6657-73; Tray of 25 | 50 mEq/20 mL; (2.5 mEq/mL) | NDC 0409-6657-01; 20 mL Single-dose Plastic Fliptop Vial
NDC 0409-6660-75; Tray of 25 | 100 mEq/40 mL; (2.5 mEq/mL) | NDC 0409-6660-01; 40 mL Single-dose Plastic Fliptop Vial

Store at 20 to 25°C (68 to 77°F). [See USP Controlled Room Temperature.]

Distributed by Hospira, Inc., Lake Forest, IL 60045 USA

LAB-1099-1.0

9/2017

PRINCIPAL DISPLAY PANEL - 20 mL Vial Label

20 mL Single-dose

CONCENTRATE
CAUTION: MUST BE DILUTED FOR INTRAVENOUS USE

14.6%
Sodium Chloride
Injection, USP
50 mEq/20 mL (2.5 mEq/mL)

PRINCIPAL DISPLAY PANEL - 20 mL Vial Tray

CONCENTRATE
CAUTION: MUST BE DILUTED FOR INTRAVENOUS USE.
20 mL Single-dose

NDC 0409-6657-73
Contains 25 of NDC 0409-6657-01
Rx only

14.6% Sodium Chloride
Injection, USP
50 mEq/20 mL (2.5 mEq/mL)

Hospira

PRINCIPAL DISPLAY PANEL - 40 mL Vial Label

40 mL Single-dose

CONCENTRATE
CAUTION: MUST BE DILUTED FOR INTRAVENOUS USE

14.6%
Sodium Chloride
Injection, USP
100 mEq/40 mL (2.5 mEq/mL)

PRINCIPAL DISPLAY PANEL - 40 mL Vial Tray

CONCENTRATE
CAUTION: MUST BE DILUTED FOR INTRAVENOUS USE.
40 mL Single-dose

NDC 0409-6660-75
Contains 25 of NDC 0409-6660-01
Rx only

14.6% Sodium Chloride
Injection, USP
100 mEq/40 mL (2.5 mEq/mL)

Hospira